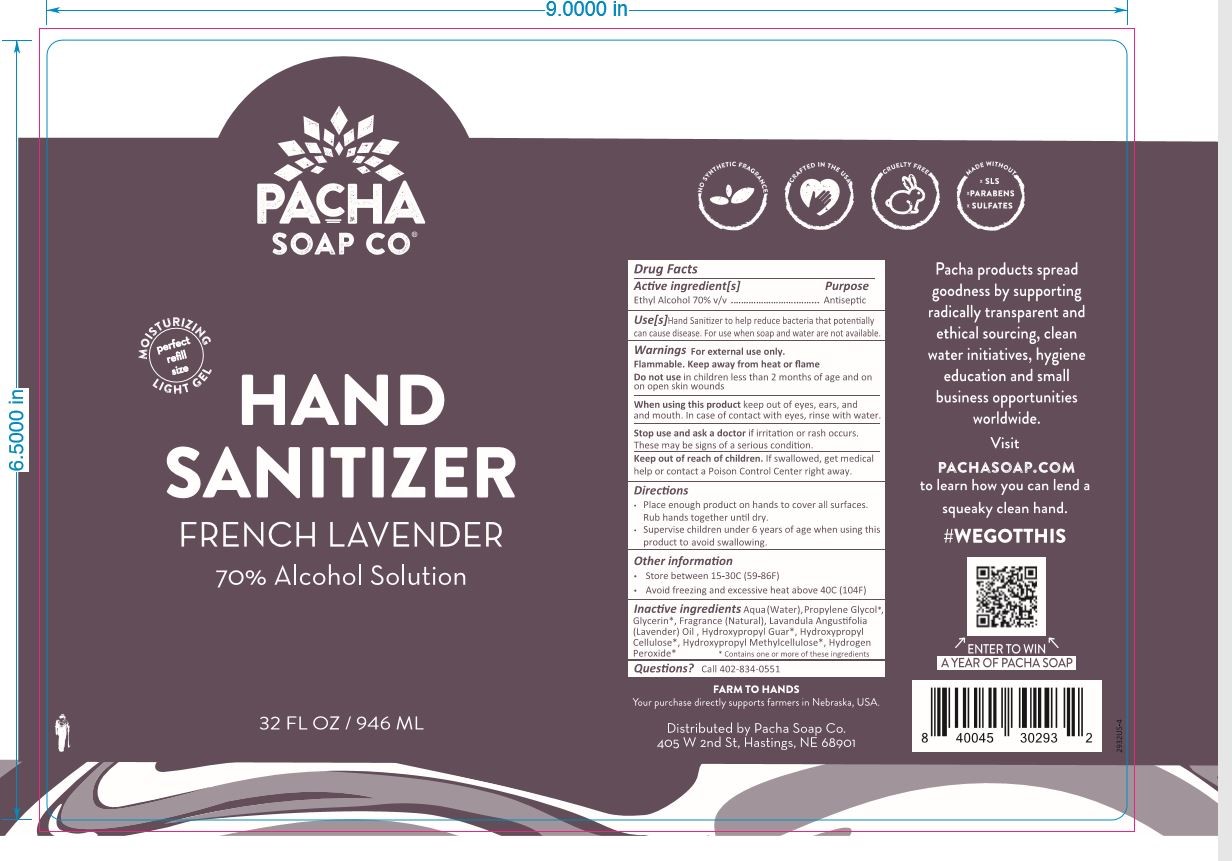 DRUG LABEL: Pacha Hand Sanitizer French Lavender
NDC: 75287-336 | Form: GEL
Manufacturer: Pacha Soap Co.
Category: otc | Type: HUMAN OTC DRUG LABEL
Date: 20200716

ACTIVE INGREDIENTS: ALCOHOL 662 mL/946 mL
INACTIVE INGREDIENTS: HYDROXYPROPYL CELLULOSE, UNSPECIFIED 9 mL/946 mL; HYDROGEN PEROXIDE 1 mL/946 mL; LAVENDER OIL 9 mL/946 mL; PROPYLENE GLYCOL 19 mL/946 mL; WATER

70% Ethanol Gel hand sanitizer with Fragrance made at PLS

Active Ingredient(s)

Ethyl Alcohol 70% v/v

Purpose

Antiseptic

Use

Hand Sanitizer to help reduce bacteria that potentially can cause disease. For use when soap and water are not available.

Warnings

For external use only. Flammable. Keep away from heat or flame

Do not use

- in children less than 2 months of age and on open skin wounds

When using this product keep out of eyes, ears, and mouth. In case of contact with eyes, rinse with water.

Stop use and ask a doctor if irritation or rash occurs. These may be signs of a serious condition.

Keep out of reach of children. If swallowed, get medical help or contact a Poison Control Center right away.

Directions

- Place enough product on hands to cover all surfaces. Rub hands together until dry.
- Supervise children under 6 years of age when using this product to avoid swallowing.

Other information

- Store between 15-30C (59-86F)
- Avoid freezing and excessive heat above 40C (104F)

Inactive ingredients

Aqua (Water), Propylene Glycol, Glycerin, Fragrance (Natural), Lavandula Angustifolia (Lavender) Oil, Hydroxypropyl Guar, Hydroxypropyl Cellulose, Hydroxypropyl Methylcellulose, Hydrogen Peroxide

Package Label - Principal Display Panel

946 mL NDC: 77017-015-32